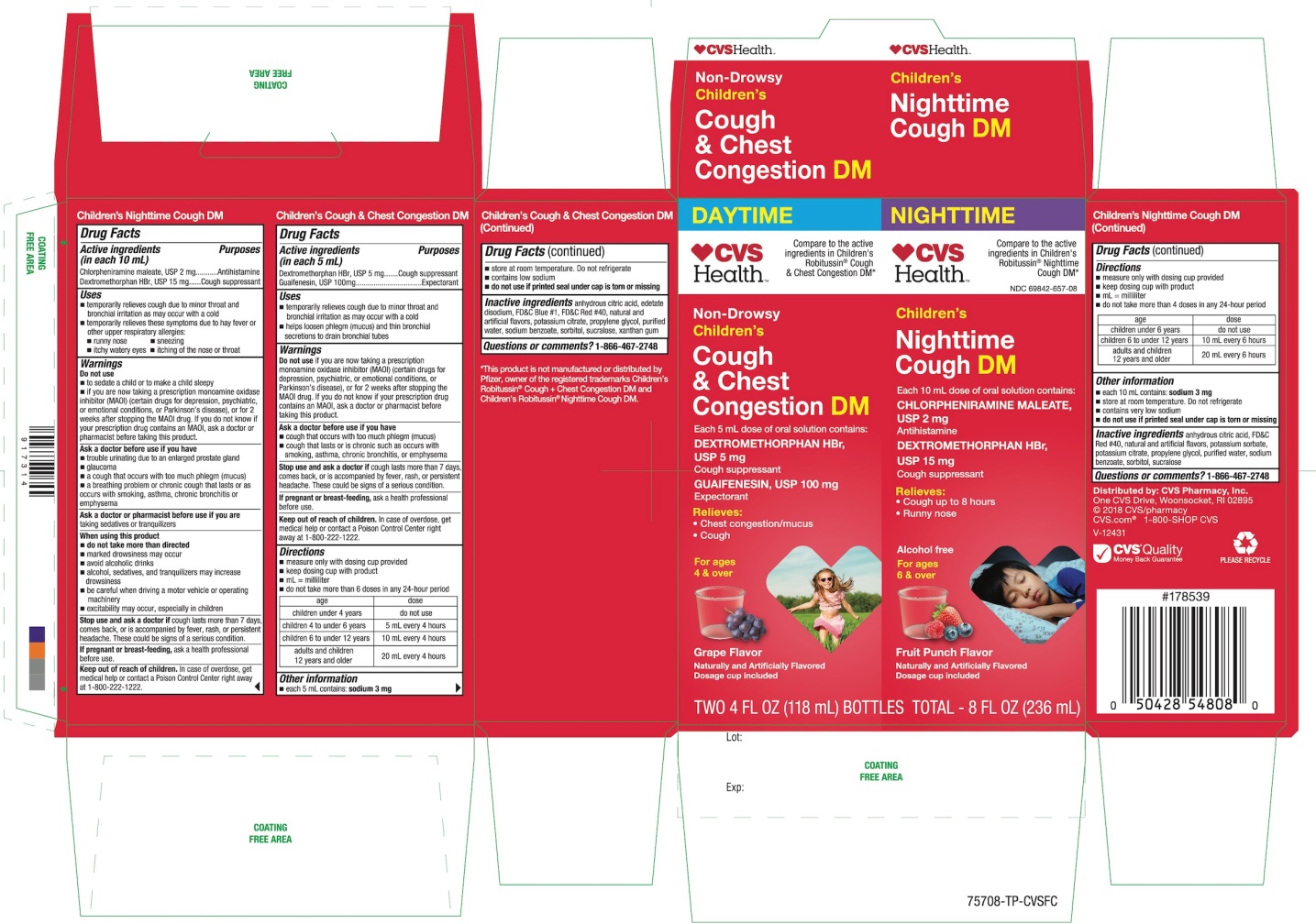 DRUG LABEL: Daytime and Nighttime Cough and Chest Congestion

NDC: 69842-657 | Form: KIT | Route: ORAL
Manufacturer: CVS Pharmacy
Category: otc | Type: HUMAN OTC DRUG LABEL
Date: 20240822

ACTIVE INGREDIENTS: DEXTROMETHORPHAN HYDROBROMIDE 5 mg/5 mL; GUAIFENESIN 100 mg/5 mL; CHLORPHENIRAMINE MALEATE 2 mg/10 mL; DEXTROMETHORPHAN HYDROBROMIDE 15 mg/10 mL
INACTIVE INGREDIENTS: ANHYDROUS CITRIC ACID; EDETATE DISODIUM; FD&C BLUE NO. 1; FD&C RED NO. 40; POTASSIUM CITRATE; PROPYLENE GLYCOL; WATER; SODIUM BENZOATE; SORBITOL; SUCRALOSE; XANTHAN GUM; ANHYDROUS CITRIC ACID; FD&C RED NO. 40; POTASSIUM SORBATE; POTASSIUM CITRATE; PROPYLENE GLYCOL; WATER; SODIUM BENZOATE; SORBITOL; SUCRALOSE

CVS Health Non-Drowsy Children’s Daytime & Night-Time Cough and Chest Congestion DM

Active ingredients Day Time (in each 5 mL)

Dextromethorphan HBr USP 5 mg

Guaifenesin. USP 100 mg

Active ingredients for Nighttime (in each 10 mL)

Chlorpheniramine maleate, USP 2 mg

Dextromethorphan HBr USP 15 mg

Purposes for Day Time

Cough suppressant

Expectorant

Purpose for Night Time

Antihistamine

Cough suppressant

Uses

DAYTIME

- temporarily relieves cough due to minor throat and bronchial irritation as may occur with a cold
- helps loosen phlegm (mucus) and thin bronchial secretions to drain bronchial tubes

NIGHTTIME

- temporarily relieves cough due to minor throat and bronchial irritation as may occur with a cold
- temporarily relieves these symptoms due to hay fever or other upper respiratory allergies:
- runny nose
- sneezing
- itching of the nose or throat
- itchy, watery eyes

Warnings

Do not us

DAYTIME

- If you are now taking a prescription monoamine oxidase inhibitor (MAOI) (certain drugs for depression, psychiatric or emotional conditions, or Parkinson's disease), or for 2 weeks after stopping the MAOI drug. If you do not know if your prescription drug contains an MAOI, ask a doctor or pharmacist before taking this product.

NIGHTTIME

- to sedate a child or to make a child sleepy
- if you are now taking a prescription monoamine oxidase inhibitor (MAOI) (certain drugs for depression, psychiatric or emotional conditions, or Parkinson's disease), or for 2 weeks after stopping the MAOI drug. If you do not know if your prescription drug contains an MAOI, ask a doctor or pharmacist before taking this product.

Ask a doctor before use if you have

DAYTIME

- cough that occurs with too much phlegm (mucus)
- cough that lasts or is chronic such as occurs with smoking, asthma, chronic bronchitis or emphysema

NIGHTTIME

- trouble urinating due to an enlarges prostate gland
- glaucoma
- a cough that occurs with too much phlegm (mucus)
- a breathing problem or chronic cough that lasts or as occurs with smoking, asthma, chronic bronchitis or emphysema

Ask a doctor or pharmacist before use if you are

NIGHTTIME

taking sedatives or tranquilizers.

When using this product

NIGHTTIME

- do not use more than directed.
- marked drowsiness may occur
- avoid alcoholic drinks
- alcohol, sedatives and tranquilizers may increase drowsiness
- be careful when driving a motor vehicle or operating machinery
- excitability may occur, especially in children

Stop use and ask a doctor if

DAYTIME

- cough last more than 7 days, comes back or is accompanied by fever, rash, or persistent headache. These could be signs of a serious condition.

NIGHTTIME

- cough last more than 7 days, comes back or is accompanied by fever, rash, or persistent headache. These could be signs of a serious condition.

If pregnant or breast-feeding,

DAYTIME

ask a health professional before use.

NIGHTTIME

ask a health professional before use

Keep out of reach of children.

DAYTIME

In case of overdose, get medical help or contact a Poison Control Center (1-800-222-1222) right away.

NIGHTTIME

In case of overdose, get medical help or contact a Poison Control Center (1-800-222-1222) right away

Directions

DAYTIME

- measure only with dosing cup provided.
- keep dosing cup with product
- mL= milliliter
- do not take more than 6 doses in any 24-hour period

age | dose
Children under 4 years | Do not use
Children 4 to under 6 years | 5 mL every 4 hours
Children 6 to under 12 years | 10 mL every 4 hours
Adults and children 12 years and older | 20 mL every 4 hours

NIGHTTIME

- measure only with dosing cup provided.
- keep dosing cup with product
- mL= milliliter
- do not take more than 4 doses in any 24-hour period

age | dose
Children under 6 years | Do not use
Children 6 to under 12 years | 10 mL every 6 hours
Adults and children 12 years and older | 20 mL every 6 hours

Other information

DAYTIME

- each 5 mL contains: sodium 3 mg
- store at room temperature. Do not refrigerate
- contain low sodium
- do not use if printed seal under cap is torn or missing

NIGHTTIME

- each 10 mL contains: sodium 3 mg
- store at room temperature. Do not refrigerate
- contain low sodium
- do not use if printed seal under cap is torn or missing

Inactive ingredients

Inactive ingredients for Day Time

anhydrous citric acid, edetate disodium, FD&C Blue # 1, FD&C Red # 40, natural and artificial flavors, potassium citrate, propylene glycol, purified water, sodium benzoate, sorbitol, sucralose, xanthan gum

Inactive ingredients for Night Time

anhydrous citric acid, FD&C Red # 40, natural and artificial flavors, potassium sorbate, potassium citrate, propylene glycol, purified water, sodium benzoate, sorbitol, sucralose

Questions or comments?

1-866-467-2748

Principal Display Panel

Compare to the active ingredients in Children's Robitussin®Cough & Chest Congestion DM*

Non-Drowsy

Children's

Cough & Chest Congestions DM

Each 5 mL dose of oral solution contains:

DEXTROMETHORPHAN HBr, USP 5 mg

Cough suppressant

GUAIFENESIN, USP 100 mg

Expectorant

Relieves

- Chest congestion/mucus
- Cough

For Ages 4 and over

Grape Flavor

Naturally and Artificially Flavored

Dosage cup included

TWO 4 FL OZ (118 mL) BOTTLES TOTAL – 8 FL OZ (236 mL)

Compare to the active ingredients in Children's Robitussin®Nighttime Cough DM*

NDC# 69842-657-08

Children's

Nighttime Cough DM

Each 10 mL dose of oral solution contains:

CHLORPHENIRAMINE MALEATE, USP 2 mg

Antihistamine

DEXTROMETHORPHAN HBr, USP 15 mg

Cough suppressant

Relieves

- Cough up to 8 hours
- Runny nose

Alcohol free

For Ages 6 & over

Fruit Punch Flavor

Naturally and Artificially Flavored

Dosage cup included

TWO 4 FL OZ (118 mL) BOTTLES TOTAL – 8 FL OZ (236 mL)

*This product is not manufactured or distributed by Pfizer, owner of the registered trademarks Children’s Robitussin®Cough + Chest Congestion DM and Children’s Robitussin®Nighttime Cough DM.

Distributed by: CVS Pharmacy, Inc.

One CVS Drive, Woonsocket, RI 02895

©2018 CVS/pharmacy

CVS.com®

1-800-SHOP CVS

V-12431

CVS®Quality

Money Back Guarantee